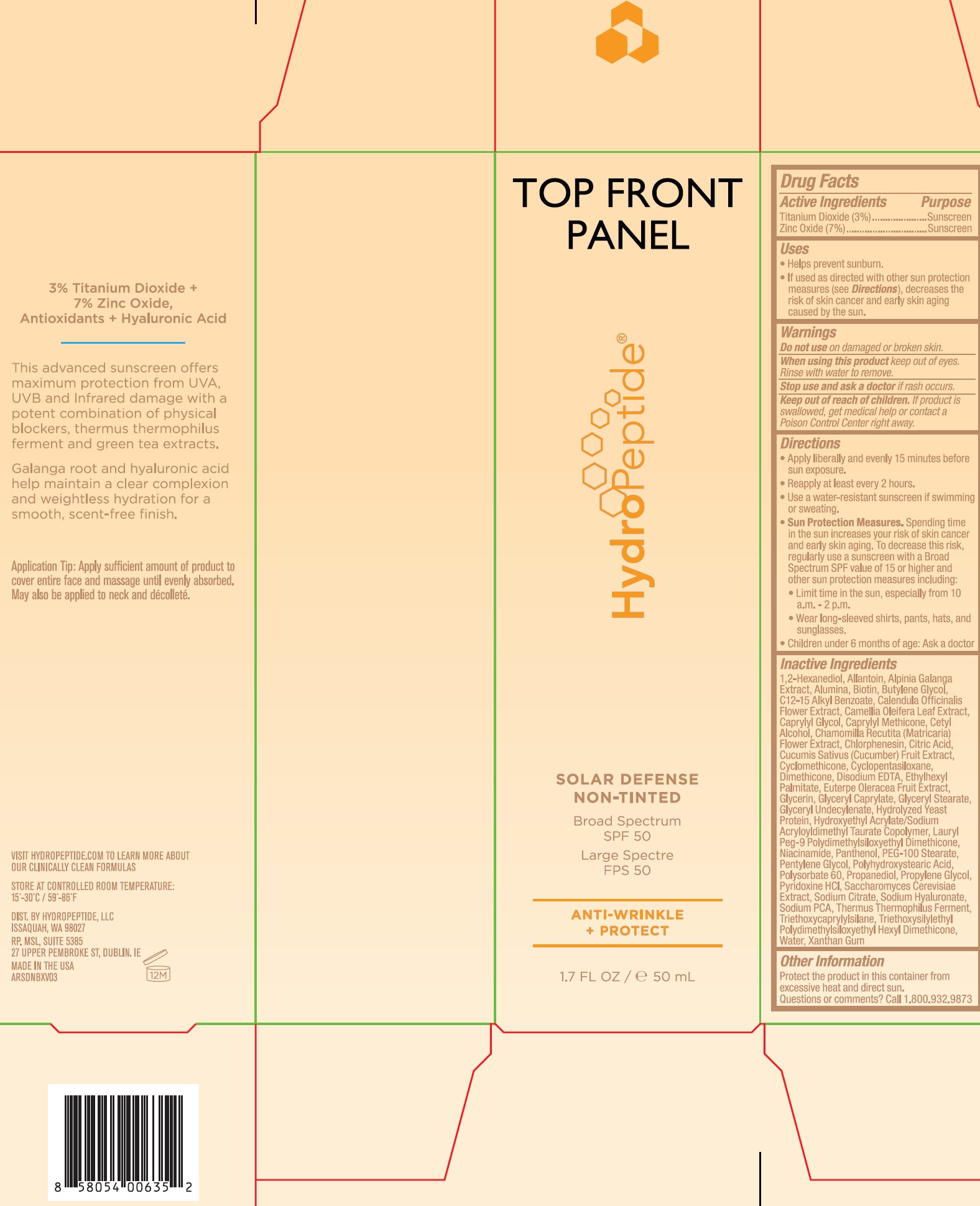 DRUG LABEL: Solar Defense Non Tinted
NDC: 60934-003 | Form: CREAM
Manufacturer: HydroPeptide LLC
Category: otc | Type: HUMAN OTC DRUG LABEL
Date: 20231209

ACTIVE INGREDIENTS: TITANIUM DIOXIDE 30 mg/1 mL; ZINC OXIDE 70 mg/1 mL
INACTIVE INGREDIENTS: 1,2-HEXANEDIOL; ALLANTOIN; ALUMINUM OXIDE; BIOTIN; BUTYLENE GLYCOL; ALKYL (C12-15) BENZOATE; CALENDULA OFFICINALIS FLOWER; CAMELLIA OLEIFERA LEAF; CAPRYLYL GLYCOL; CAPRYLYL TRISILOXANE; CETYL ALCOHOL; CHAMOMILE; CHLORPHENESIN; CUCUMBER; CYCLOMETHICONE; DIMETHICONE; EDETATE DISODIUM ANHYDROUS; ETHYLHEXYL PALMITATE; ACAI; GLYCERIN; GLYCERYL CAPRYLATE; GLYCERYL MONOSTEARATE; GLYCERYL 1-UNDECYLENATE; LAURYL PEG-9 POLYDIMETHYLSILOXYETHYL DIMETHICONE; NIACINAMIDE; PANTHENOL; PEG-100 STEARATE; PENTYLENE GLYCOL; POLYSORBATE 60; PROPANEDIOL; PROPYLENE GLYCOL; PYRIDOXINE HYDROCHLORIDE; SACCHAROMYCES CEREVISIAE; SODIUM CITRATE; HYALURONATE SODIUM; SODIUM PYRROLIDONE CARBOXYLATE; THERMUS THERMOPHILUS LYSATE; TRIETHOXYCAPRYLYLSILANE; WATER; XANTHAN GUM

Solar Defense Non-Tinted

Active Ingredients

Titanium Dioxide (3%)

Zinc Oxide (7%)

Purpose

Sunscreen

Uses

- Helps prevent sunburn.
- If used as directed with other usn protection measures (see), decreases the risk of skin cancer and early skin aging caused by the sun. Directions

Warnings

Do not use

on damaged or broken skin.

When using this product

Keep out of eyes. Rinse with water to remove.

Stop use and ask a doctor

if rash occurs.

Keep out of reach of children.

If product is swallowed, get medical help or contact a Poison Control Center right away.

Directions

- Apply liberally and evenly 15 minutes before sun exposure.
- Reapply at least every 2 hours.
- Use a water-resistant sunscreen if swimming or sweating.
- Spending time in the sun increases your risk of skin cancer and early skin aging. To decrease this risk, regularly use a suncreen with a Broad Spectrum SPF value of 15 or higher and other sun protection measures including: Sun Protection Measures.
- Limit time in the sun, especially from 10 a.m. - 2 p.m.
- Wear long-sleeved shirts, pants, hats, and sunglasses.
- Children under 6 months of age: Ask a doctor

Inactive Ingredients

1,2-Hexanediol, Allantoin, Alpinia Galanga Extract, Alumina, Biotin, Butylene Glycol, C12-15 Alkly Benzoate, Calendula Officinalis Flower Extract, Camellia Oleifera Leaf Extract, Caprylyl Glycol, Caprylyl Methicone, Cetyl Alcohol, Chamomilla Recutita (Matricaria) Flower Extract, Chlorphenesin, Citric Acid Cucumis Sativus (Cucumber) Fruit Extract, Cyclomethicone, Cyclophentasiloxane, Dimethicone, Disodium EDTA, Ethylhexyl Palmitate, Euterpe Oleracea Fruit Extract, Glycerin, Glyceryl Caprylate, Glyceryl Stearate, Glyceryl Undecylenate, Hydrolyzed Yeast Protein, Hydroxyethyl Acylate/Sodium Acryloyldimethyl Taurate Copolymer, Lauryl Peg-9 Polydimethylsiloxyethyl Dimethicone, Niacinamide, Panthenol, PEG-100 Stearate, Pentylene Glycol, Polyhydroxystearic Acid, Polysorbate 60, Propanediol, Propylene Glycol, Pyridoxine HCl, Saccharomyces Cerevisiae Extract, Sodium Citrate, Sodium Hyaluronate, Sodium PCA, Thermus Thermophilus Ferment, Triethoxycaprylylsilane, Triethoxysilylethyl Polydimethylsiloxyethyl Hexyl Dimethicone, Water, Xanthan Gum

Other Information

Protect the product in this container from excessive heat and direct sun.

Questions or comments?

Call 1.800.932.9873